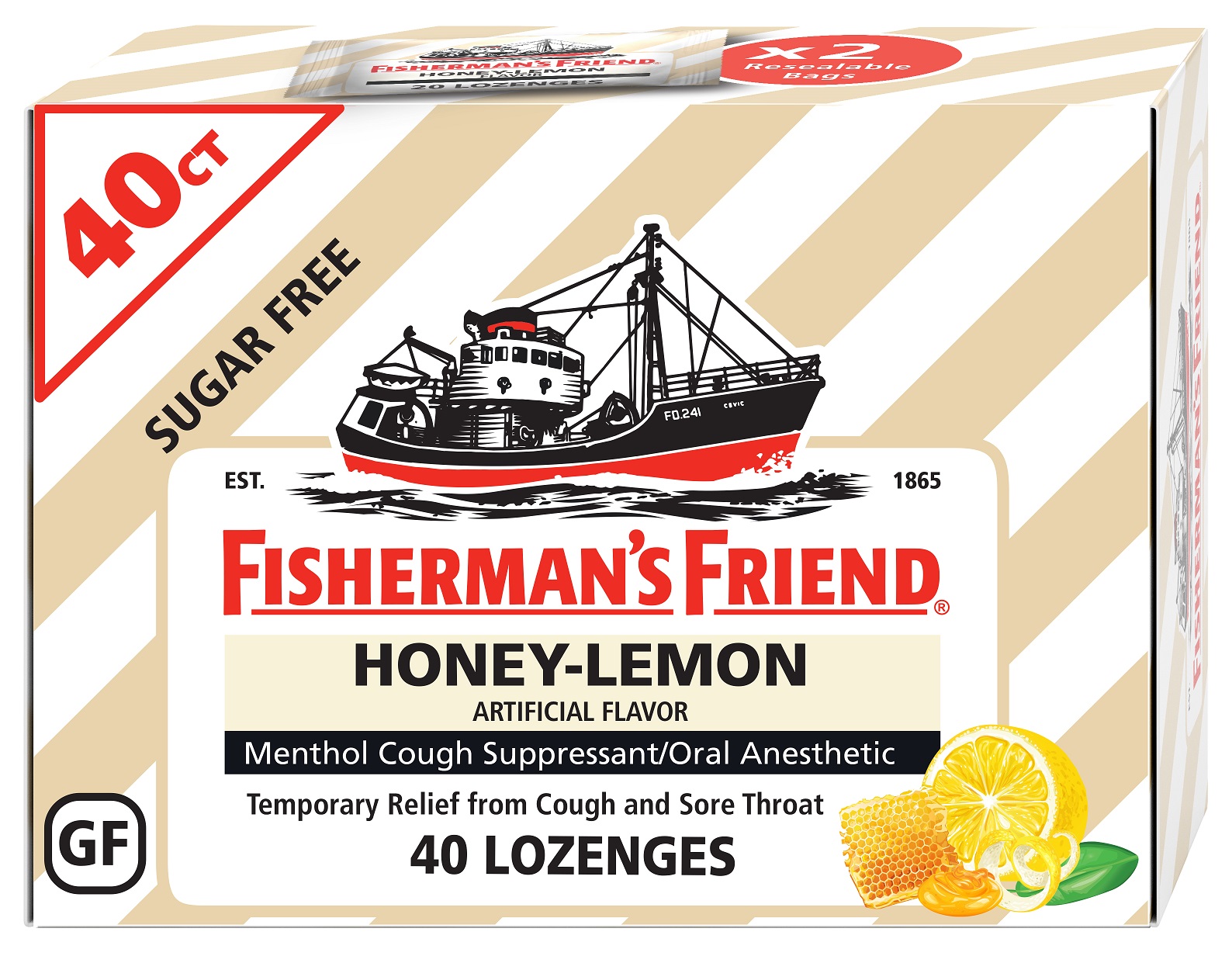 DRUG LABEL: Sugar Free Honey-Lemon Fishermans Friend Menthol Cough Suppressant
NDC: 55711-071 | Form: LOZENGE
Manufacturer: Lofthouse of Fleetwood, Ltd.
Category: otc | Type: HUMAN OTC DRUG LABEL
Date: 20250327

ACTIVE INGREDIENTS: MENTHOL 5.52 mg/1 1
INACTIVE INGREDIENTS: MAGNESIUM STEARATE; SORBITOL; ACESULFAME; CITRIC ACID ACETATE; SUCRALOSE

Honey Lemon

Active ingredient (in each lozenge)

Menthol 5.52 mg

Purpose

Cough suppressant/oral anesthetic.

Uses

temporarily relieves • occasional minor sore throat • cough due to minor throat and bronchial irritation occuring with the common cold or inhaled irritants

Warnings

Sore throat warning: Severe or persistent sore throat or sore throat that occurs with high fever, headache, nausea, and vomiting may be serious. Ask a doctor right away. Do not use more than 2 days or give to children under 2 years of age unless directed by a doctor.

Ask Doctor

Ask a doctor before use if you have • a cough that occurs with too much phlegm (mucus) • a persistent or chronic cough that lasts such as occurs with smoking, asthma, or emphysema.

When Using

When using this product do not use more than directed.

Stop Use

Stop use and ask a doctor if • cough lasts more than 7 days, comes back, or occurs with fever, rash, or headache that lasts. These could be signs of a serious condition. • sore throat is severe, lasts more than 2 days, is accompanied or followed by fever, headache, rash, swelling, nausea, or vomiting.

Pregnant or Breast Feeding

If pregnant or breast-feeding, ask a health prefessional before use.

Keep Out of Reach of Children

Directions

• adults and children 2 years of age and over: allow 1 lozenge to dissolve slowly in the mouth • repeat every 2 hours as needed or as directed by a doctor • children under 2 years of age: ask a doctor

Inactive Ingredients

Inactive ingredients acesulfame K, citric acid, honey lemon flavor, magnesium stearate, sorbitol, sucralose.

PACKAGE LABEL

FISHERMAN'S FRIEND

HONEY-LEMON

Menthol Cough Suppressant/Oral Anesthetic

SUGAR FREE

40 CT

Manufactured by: Lofthouse of Fleetwood Ltd., Lancs, England

Distributed by: Greenwood Brands, LLC, Buffalo-Niagra, NY 14225

ffinfo@greenwoodg.com